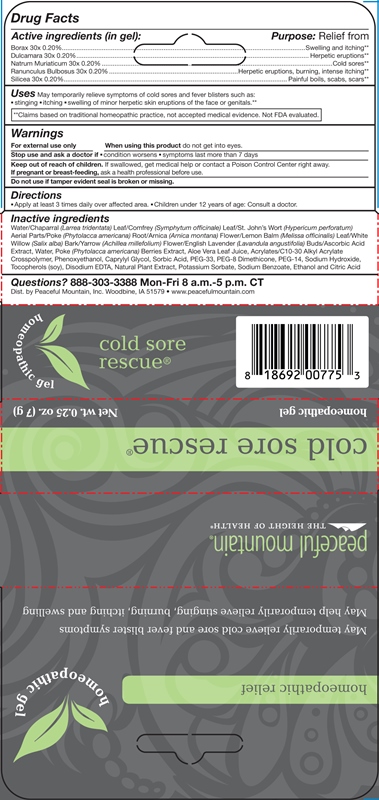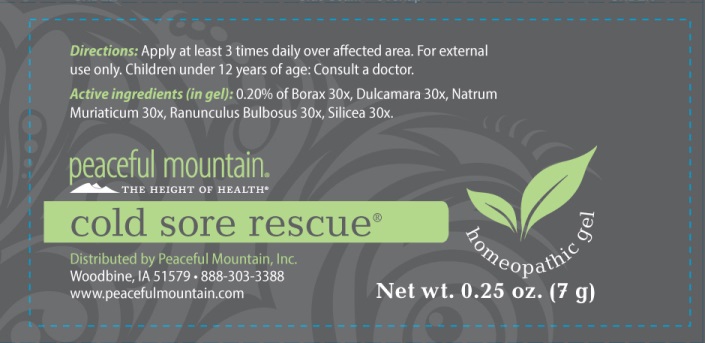 DRUG LABEL: Cold Sore Rescue
NDC: 43846-0031 | Form: GEL
Manufacturer: Peaceful Mountain, Inc.
Category: homeopathic | Type: HUMAN OTC DRUG LABEL
Date: 20240613

ACTIVE INGREDIENTS: SODIUM BORATE 30 [hp_X]/1 g; SOLANUM DULCAMARA TOP 30 [hp_X]/1 g; SODIUM CHLORIDE 30 [hp_X]/1 g; RANUNCULUS BULBOSUS WHOLE 30 [hp_X]/1 g; SILICON DIOXIDE 30 [hp_X]/1 g
INACTIVE INGREDIENTS: ALOE VERA LEAF; ARNICA MONTANA FLOWER; CARBOMER HOMOPOLYMER TYPE C; LARREA TRIDENTATA LEAF; COMFREY LEAF; EDETATE DISODIUM; LAVANDULA ANGUSTIFOLIA FLOWER; MELISSA OFFICINALIS LEAF; OREGANO; POLYETHYLENE GLYCOL 1600; PEG-8 DIMETHICONE; POLYETHYLENE GLYCOL 700; PHENOXYETHANOL; CAPRYLYL GLYCOL; SORBIC ACID; PHYTOLACCA AMERICANA FRUIT; PHYTOLACCA AMERICANA ROOT; POTASSIUM SORBATE; WATER; SODIUM HYDROXIDE; ST. JOHN'S WORT; ASCORBIC ACID; .ALPHA.-TOCOPHEROL; SALIX ALBA BARK; ACHILLEA MILLEFOLIUM FLOWER; CITRIC ACID MONOHYDRATE; ALCOHOL; SODIUM BENZOATE

DRUG FACTS:

ACTIVE INGREDIENTS:

(in gel): 0.20% of BORAX 30X, DULCAMARA 30X, NATRUM MURIATICUM 30X, RANUNCULUS BULBOSUS 30X, SILICEA 30X.

USES:

May temporary relief symptoms of cold sores and fever blisters such as: stinging - itching - swelling of minor herpatic skin eruptions of the face or genitals.**

**Claims based on traditional homeopathic practice, not accepted medical evidence. Not FDA evaluated.

WARNINGS:

For external use only.

When using this product - Do not get into eyes.

Stop use and ask a doctor if: Condition worsens - Symptoms last more than 7 days

Keep out of reach of children. If swallowed, get medical help or contact a Poison Control Center right away.

If pregnant or breast-feeding, ask a health professional before use.

Do not use if tamper evident seal is broken or missing.

Keep out of reach of children. If swallowed, get medical help or contact a Poison Control Center right away.

DIRECTIONS:

Apply at least 3 times daily over affected area. Children under 12 years of age: Consult a doctor.

USES:

May temporary relief symptoms of cold sores and fever blisters such as: stinging - itching - swelling of minor herpatic skin eruptions of the face or genitals.**

**Claims based on traditional homeopathic practice, not accepted medical evidence. Not FDA evaluated.

INACTIVE INGREDIENTS:

Water, Chaparral (Larrea Tridentata) Leaf, Comfrey (Symphytum Officinale) Leaf, St. John’s Wort (Hypericum Perforatum) Aerial Parts, Poke (Phytolacca Americana) Root, Arnica (Arnica Montana) Flower, Lemon Balm (Melissa Officinalis) Leaf, White Willow (Salix Alba) Bark, Yarrow (Achillea Millefolium) Flower, English Lavender (Lavandula Angustifolia) Buds, Ascorbic Acid, Poke (Phytolacca Americana) Berries, Aloe Vera 10X Concentrate, Acrylates/C10-30 Alkyl Acrylate Crosspolymer, Phenoxyethanol, Caprylyl Glycol, Sorbic Acid, PEG-33, PEG-8 Dimethicone, PEG-14, Sodium Hydroxide, Tocopherols (Soy), Edetate Disodium (EDTA), Natural Plant Extract (Origanox WS), Potassium Sorbate, Sodium Benzoate, Alcohol, Citric Acid.

QUESTIONS:

888-303-3388 Mon-Fri 8 a.m.-5 p.m. CT

Dist. by Peaceful Mountain, Inc., Woodbine, IA 51579

www.peacefulmountain.com

PACKAGE LABEL DISPLAY:

homeopathic relief

May temporarily relieve cold sore and fever blisters symptoms

May help temporarily relieve stinging, burning, itching and swelling

peaceful mountain

THE HEIGHT OF HEALTH

formulated in boulder, co

cold sore rescue

homeopathic gel

Net wt. 0.25 oz. (7 g)